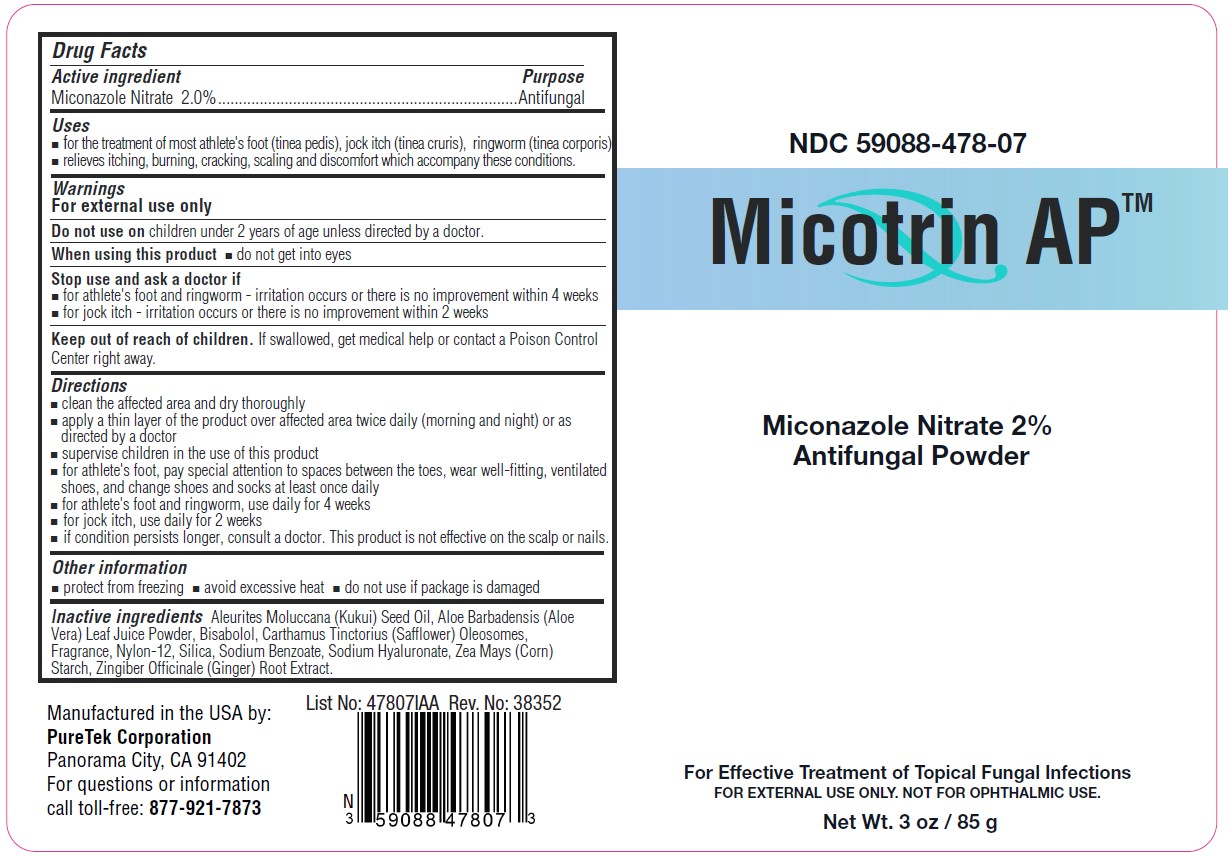 DRUG LABEL: Micotrin AP
NDC: 59088-478 | Form: POWDER
Manufacturer: PureTek Corporation
Category: otc | Type: HUMAN OTC DRUG LABEL
Date: 20241001

ACTIVE INGREDIENTS: MICONAZOLE NITRATE 2 g/85 g
INACTIVE INGREDIENTS: LEVOMENOL; CARTHAMUS TINCTORIUS (SAFFLOWER) OLEOSOMES; SILICON DIOXIDE; SODIUM BENZOATE; HYALURONATE SODIUM; STARCH, CORN; GINGER; ALOE VERA LEAF; NYLON-12; KUKUI NUT OIL

Micotrin AP™
10/19- Updatinf to new marketing date v3

Active ingredient

Miconazole Nitrate 2.0%

Purpose

Antifungal

Uses

- for the treatment of most athlete's foot (tinea pedis), jock itch (tinea cruris), ringworm (tinea corporis)
- relieves itching, burning, cracking, scaling and discomfort which accompany these conditions.

WARNINGS

For external use only.

Do not use on

children under 2 years of age unless directed by a doctor

When using this product

- do not get into eyes

Stop use and ask a doctor if

- for athlete's foot and ringworm - irritation occurs or there is no improvement within 4 weeks
- for jock itch - irritation occurs or there is no improvement within 2 weeks

Keep out of reach of children.

If swallowed, get medical help or contact a Poison Control Center right away.

Directions

- clean the affected area and dry thoroughly
- apply a thin layer of the product over affected area twice daily (morning and night) or as directed by a doctor
- supervise children in the use of this product
- for athlete's foot, pay special attention to spaces between the toes, wear well-fitting, ventilated shoes, and change shoes and socks at least once daily
- for athlete's foot and ringworm, use daily for 4 weeks
- for jock itch, use daily for 2 weeks
- if condition persists longer, consult a doctor. This product is not effective on the scalp or nails.

Other information

■ protect from freezing ■ avoid excessive heat ■ do not use if package is damaged

Inactive ingredients

Aleurites Moluccana (Kukui) Seed Oil, Aloe Barbadensis (Aloe Vera) Leaf Juice Powder, Bisabolol, Carthamus Tinctorius (Safflower) Oleosomes, Fragrance, Nylon-12, Silica, Sodium Benzoate, Sodium Hyaluronate, Zea Mays (Corn) Starch, Zingiber Officinale (Ginger) Root Extract.